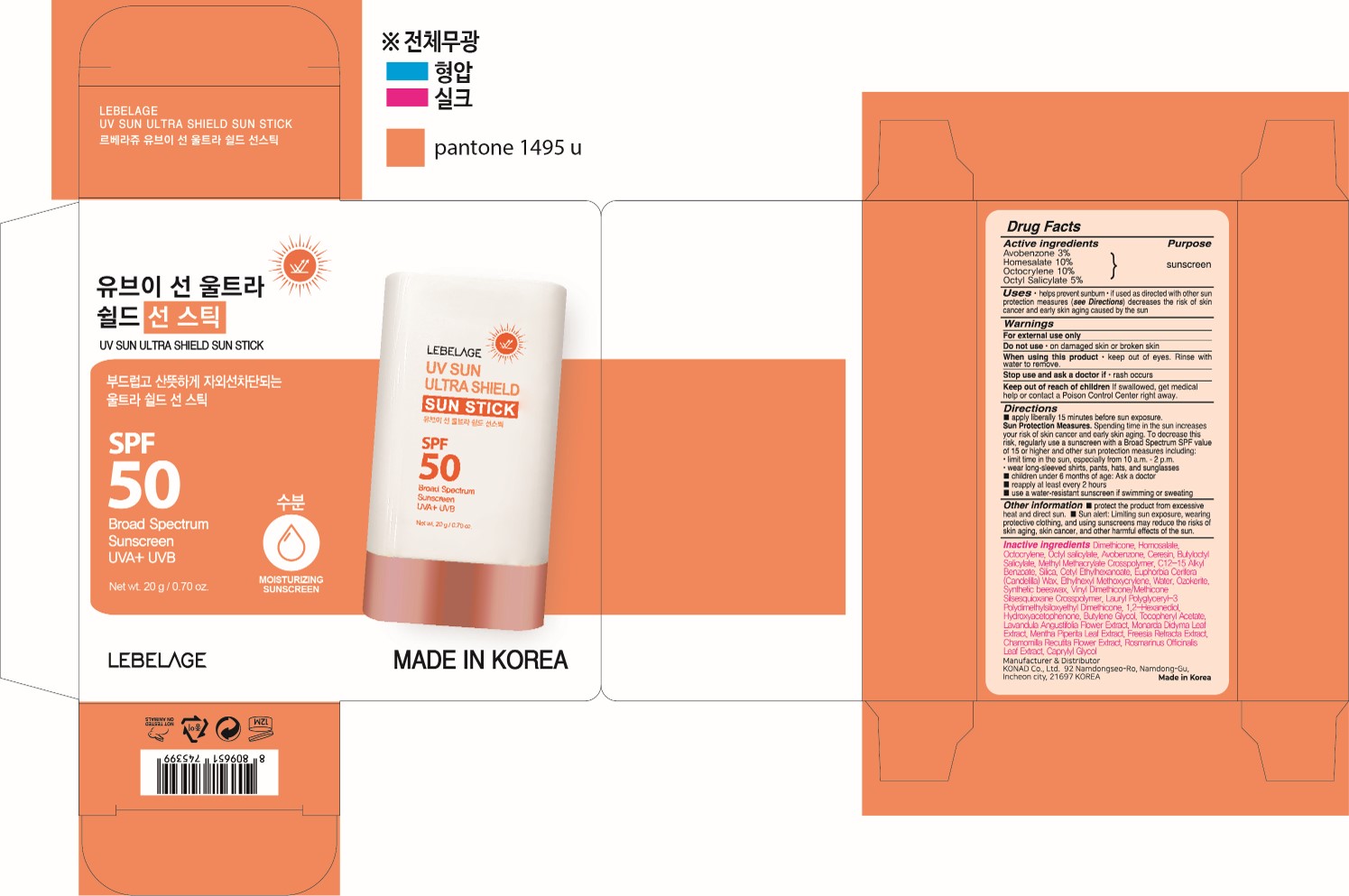 DRUG LABEL: LEBELAGE UV SUN ULTRA SHIELD SUNSTICK
NDC: 85948-010 | Form: STICK
Manufacturer: DONGDONGGURIMOO CO.,LTD.
Category: otc | Type: HUMAN OTC DRUG LABEL
Date: 20250714

ACTIVE INGREDIENTS: OCTISALATE 1 g/20 g; OCTOCRYLENE 2 g/20 g; HOMOSALATE 2 g/20 g; AVOBENZONE 0.6 g/20 g
INACTIVE INGREDIENTS: BUTYLENE GLYCOL; CETYL ETHYLHEXANOATE; SYNTHETIC BEESWAX; VINYL DIMETHICONE/METHICONE SILSESQUIOXANE CROSSPOLYMER; CERESIN; HYDROXYACETOPHENONE; ETHYLHEXYL METHOXYCRYLENE; 1,2-HEXANEDIOL; MONARDA DIDYMA LEAF; DIMETHICONE; ROSEMARY; C12-15 ALKYL BENZOATE; EUPHORBIA CERIFERA (CANDELILLA) WAX; ALPHA-TOCOPHEROL ACETATE; BUTYLOCTYL SALICYLATE; SILICA; WATER

DONGDONGGURIMOO CO.,LTD_UV SUN ULTRA SHIELD SUN STICK

Active ingredients

Avobenzone 3%

Homosalate 10%

Octocrylene 10%

Octyl Salicylate 5%

Purpose

sunscreen

Uses

• helps prevent sunburn

• if used as directed with other sun protection measures (see Directions) decreases the risk of skin cancer and early skin aging caused by the sun.

Warnings

For external use only

Do not use

· on damaged skin or broken skin.

When using this product

· keep out of eyes. Rinse with water to remove.

Stop use and ask a doctor if

· rash occurs.

Keep out of reach of children

If swallowed, get medical help or contact Poison Control Center right away.

Directions

■ Apply liberally 15 minutes before sun exposure.
Sun Protection Measures. Spending time in the sun increases your risk of skin cancer and early skin aging. To decrease this risk, regularly use a sunscreen with a Broad Spectrum SPF value of 15 or higher and other sun protection measures including:
·limit time in the sun, especially from 10 a.m. – 2 p.m.
·wear long-sleeved shirts, pants, hats, and sunglasses
■ Children under 6 months of age: Ask a doctor
■ Reapply at least every 2 hours.
■ Use a water-resistant sunscreen if swimming or sweating.

Other information

■ Protect the product in this container form excessive heat or direct sun. ■ Sun alert: Limiting sun exposure, wearing protective clothing, and using sunscreens may reduce the risks of skin aging, skin cancer, and other harmful effects of the sun.

Inactive ingredients

Dimethicone, Ceresin, Butyloctyl Salicylate, Methyl Methacrylate Crosspolymer, C12-15 Alkyl Benzoate, Silica, Cetyl Ethylhexanoate, Euphorbia Cerifera (Candelilla) Wax, Ethylhexyl Methoxycrylene, Water, Ozokerite, Synthetic Beeswax, Vinyl Dimethicone/Methicone Silsesquioxane Crosspolymer, Lauryl Polyglyceryl-3 Polydimethylsiloxyethyl Dimethicone, 1,2-Hexanediol, Hydroxyacetophenone, Butylene Glycol, Tocopheryl Acetate, Lavandula Angustifolia Flower Extract, Monarda Didyma Leaf Extract, Mentha Piperita Leaf Extract, Freesia Refracta Extract, Chamomilla Recutita Flower Extract, Rosmarinus Officinalis Leaf Extract, Caprylyl Glycol